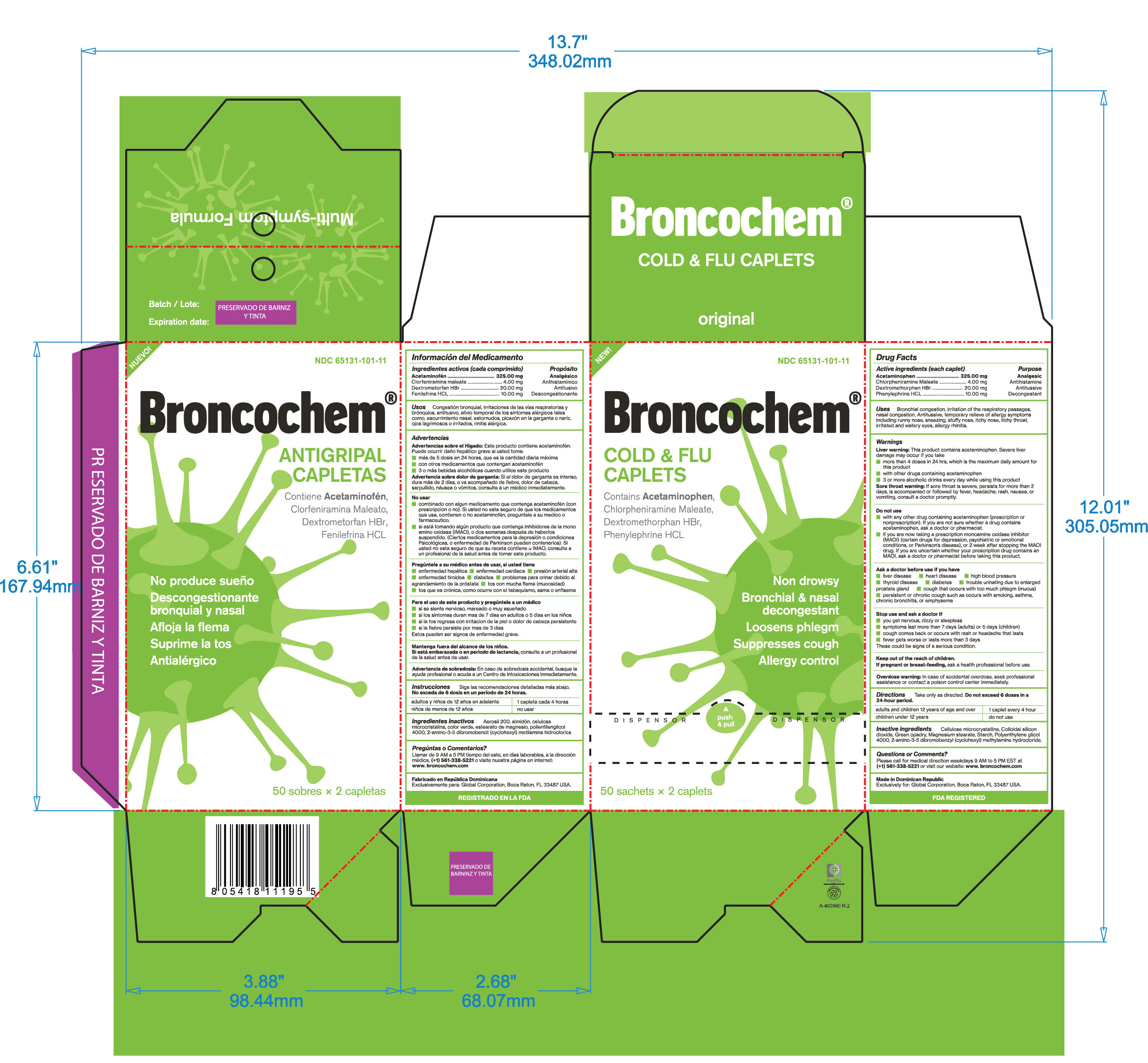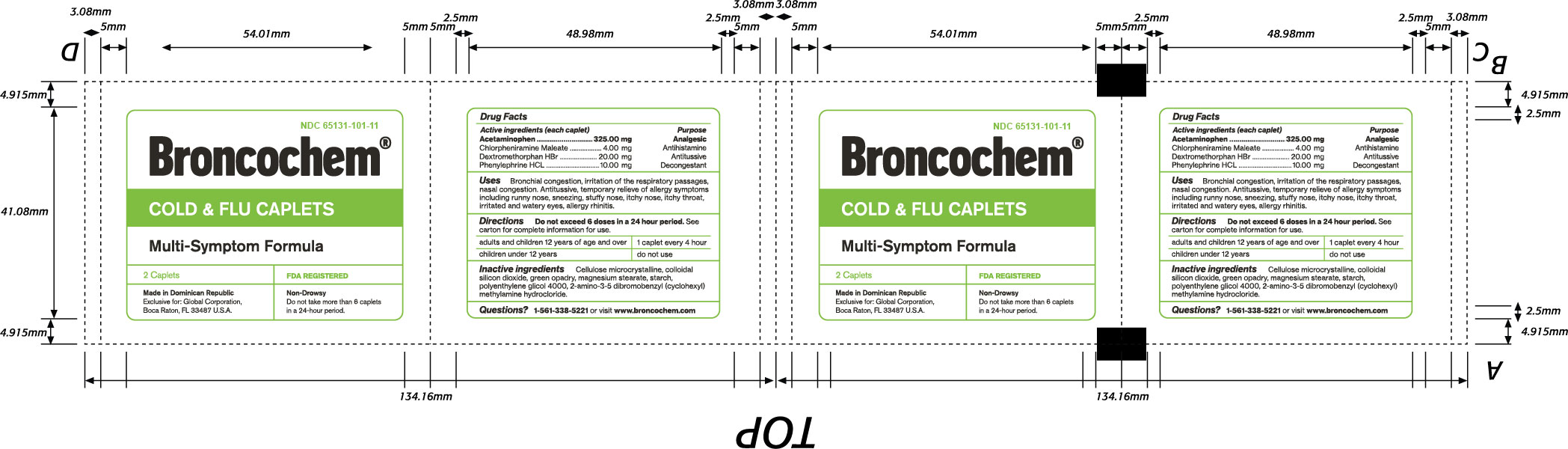 DRUG LABEL: BRONCOCHEM
NDC: 65131-101 | Form: TABLET, COATED
Manufacturer: LABORATORIO MAGNACHEM INTERNATIONAL SRL
Category: otc | Type: HUMAN OTC DRUG LABEL
Date: 20250323

ACTIVE INGREDIENTS: ACETAMINOPHEN 325 mg/1 1; DEXTROMETHORPHAN HYDROBROMIDE 20 mg/1 1; PHENYLEPHRINE HYDROCHLORIDE 10 mg/1 1; CHLORPHENIRAMINE MALEATE 4 mg/1 1
INACTIVE INGREDIENTS: CELLULOSE, MICROCRYSTALLINE 250 mg/1 1; STARCH, PREGELATINIZED CORN 142 mg/1 1; SILICON DIOXIDE 2 mg/1 1; MAGNESIUM STEARATE 2.8 mg/1 1; PEG-80 STEARATE 1.6 mg/1 1

BRONCOCHEM COLD & FLU CAPLETS

Warnings

Unless directed by a physician do not take this product if persistent or chronic cough such as occurs with, smoking, asthma, chronic bronchitis, emphysema, or if cough is accompained by excessive phlem (mucus). Likewise if you have heart disease, diabetes, or difficulty in urination due to enlargement of the prostate gland, do not take this product unless directed by a physician.

If nervousness, dizziness, or sleeplessness occurs, discontinue use or consult a doctor.

If symptoms do not improve within 7 days or are accompanied by fever, consult a doctor.

A persistent cough may be a sign of a serius condition. If cough or other symptoms persist or not improve with any drug, if you are pregnant or nursing a baby, seeh the advice of a health professional before using this product.

Unless directed by a doctor, do not take this product if you are presently taking another product containing pseudoephedryne HCl, or if you are taking this product precaution must be taken when driving a motor vehicle or operating machinery.

Active Ingredients

Acetaminofen

Dextromethorphan HBr

Phenylephryne HCL

Chlorpheniramine Maleate

Purpose

Analgesic

Antihistaminic

Antitussive

Descongestant

Keep Out Of The Reach Of Children

In case of accidental overdose, seek professional assistance or contact a poison control center immediately

Indications and Usage

Bronchial congestion, irritation of the respiratory passages, nasal congestion.

Antitussive, temporary reliev of allergy symptoms including runny nose, sneezing, stuffy nose, itchy nose, itchy throat, irritated and watery eyes, allergy rhinitis

Indications and Usage

Adults and children 12 years and over, take one tablet every 4 hours.

Do not exceed 6 doses in a 24 hour period

Drug Interactions

Do not use if you are taking a prescription monoamine oxidase inhibitor (MAOI), (Certain drugs for depression, psychiatric or emotional conditions, or Parkinsons disease) or for 2 weeks after stopping that MAOI drug, if you are uncertain whether your prescription drug contains an MAOI, consult a health professional before taking this product

Inactive Ingredients

Cellulose Microcrystalline, Colloidal Silicon dioxide, Green Opadry, Magnesium Stearate, Pregelatinized Starch, PEG 4000